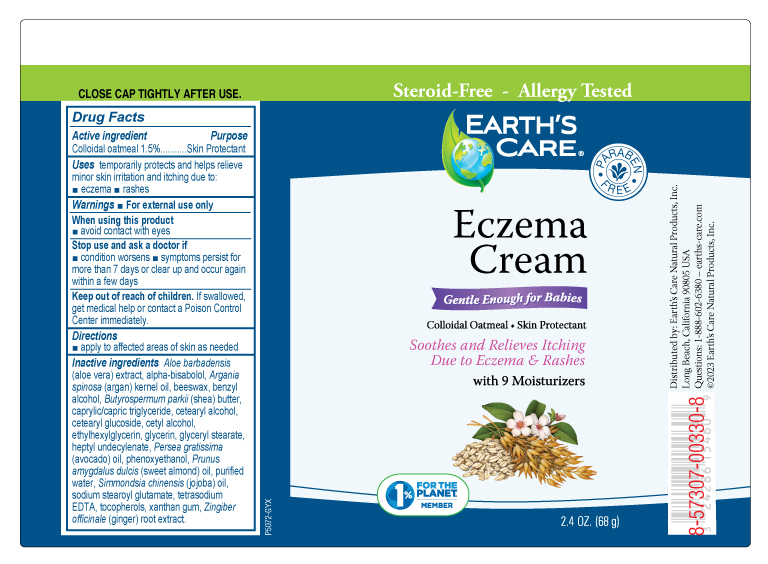 DRUG LABEL: EARTHS CARE Eczema Cream
NDC: 24286-1579 | Form: CREAM
Manufacturer: DLC Laboratories, Inc.
Category: otc | Type: HUMAN OTC DRUG LABEL
Date: 20260209

ACTIVE INGREDIENTS: OATMEAL 1.5 g/100 g
INACTIVE INGREDIENTS: AVOCADO OIL 0.5 g/100 g; CAPRYLIC/CAPRIC/LINOLEIC TRIGLYCERIDE 6.5 g/100 g; ALMOND OIL 1.5 g/100 g; EDETATE SODIUM 0.1 g/100 g; TOCOPHEROL 0.1 g/100 g; XANTHAN GUM 0.5 g/100 g; WHITE WAX 4 g/100 g; GINGER 0.05 g/100 g; SHEA BUTTER 1 g/100 g; SODIUM STEAROYL GLUTAMATE 0.4 g/100 g; CETYL ALCOHOL 2.5 g/100 g; GLYCERIN 3 g/100 g; GLYCERYL STEARATE SE 3.8 g/100 g; ALOE VERA LEAF POLYSACCHARIDES 0.01 g/100 g; HEPTYL UNDECYLENATE 6 g/100 g; .ALPHA.-BISABOLOL, (+)- 0.1 g/100 g; CETEARYL GLUCOSIDE 3 g/100 g; PHENOXYETHANOL 0.9 g/100 g; ETHYLHEXYLGLYCERIN 0.2 g/100 g; BENZYL ALCOHOL 1 g/100 g; ARGAN OIL 0.1 g/100 g; JOJOBA OIL 0.1 g/100 g; WATER 63.14 g/100 g

EARTH'S CARE® Eczema Cream

Active Ingredient

Colloidal oatmeal 1.5%

Purpose

Skin Protectant

Uses

temporarily protects and helps relieve minor skin irritation and itching due to:

eczema

rashes

Warnings

For external use only

When using this product

avoid contact with eyes

Stop use and ask a doctor if

condition worsens

symptoms persist for more than 7 days or clear up and occure again within a few days

Keep out of reach of children

If swallowed, get medical help or contact a Poison Control Center immediately

Directions

apply to affected area of skin as needed

Inactive ingredients

Aloe barbadensis(aloe vera) extract, alpha-bisabolol, Argania spinosa (argan) kernel oil, beeswax, benzyl alcohol, Butyrospermum parkii (shea) butter, caprylic/capric triglyceride, ceteary alcohol, cetearyl glucoside, cetyl alcohol, ethylhexylglycerin, glycerin, glyceryl stearate, heptyl undecylenate, Persea gratissima (avocado) oil, phenoxyethanol, Prunus amygdalus dulcis (sweet almond) oil, purified water, simmondsia chinensis (jojoba) oil, sodium stearoyl glutamate, tetrasodium EDTA, tocopherols. xanthan gum, Zingiber officinale (ginger) root extract

Questions

1-888-602-6380-earths-care.com

©2023 Earth's Care Natural Product, Inc.

Distributed by:

Earth's Care Natural Products, Inc.

Long Beach, California 90805 USA

PACKAGE LABEL

Steroid-Free-Allergy Tested

EARTH'S

CARE®

PARABEN

FREE

Eczema

Cream

Gentle Enough for Babies

Colloidal Oatmeal • Skin Protectant

Soothes and Relieves Itching

Due to Eczema & Rashes

with 9 Moisturizers

1% For the

Planet

Member

2.4 OZ (68g)